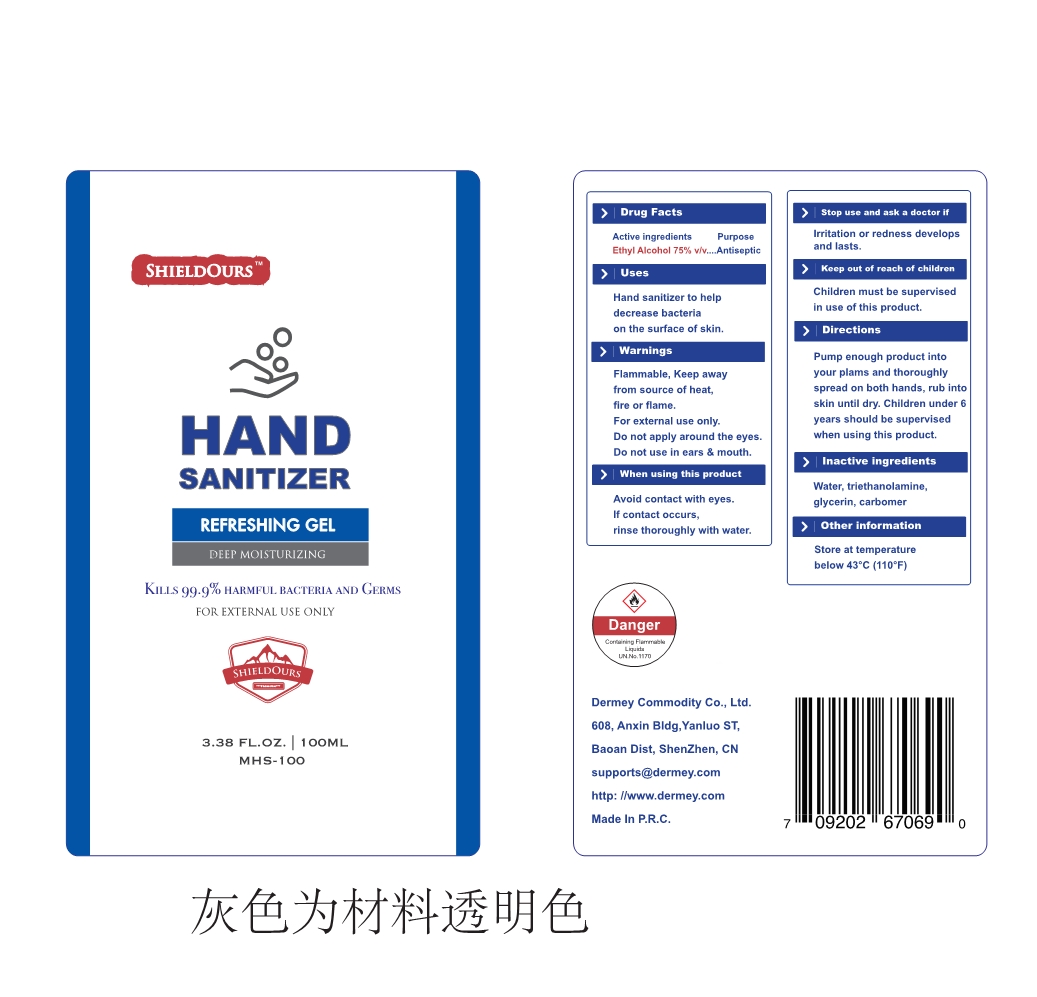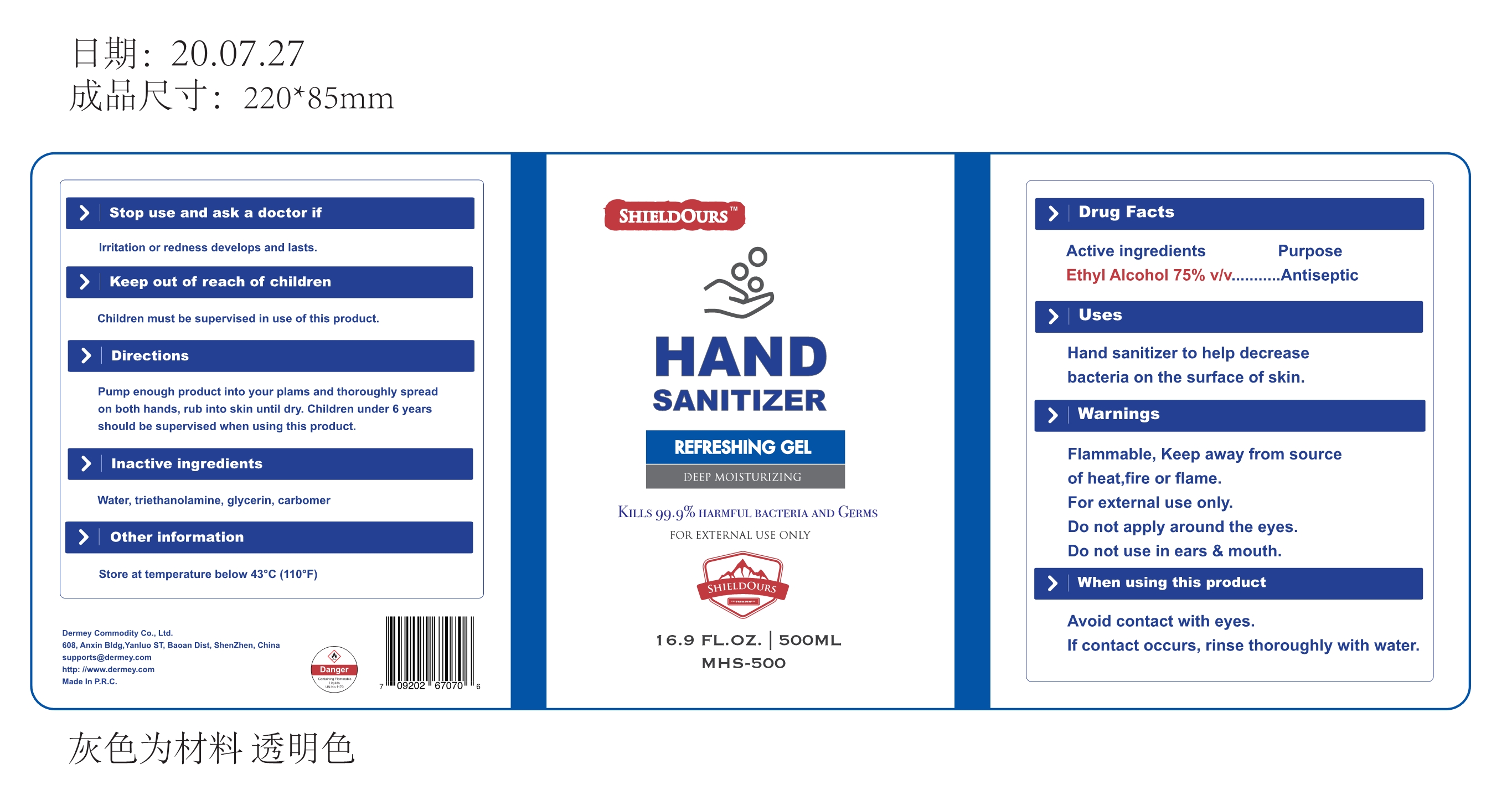 DRUG LABEL: Wash-free hand sanitizer
NDC: 55028-015 | Form: GEL
Manufacturer: Zhongshan Dermey Commodity Co., Ltd.
Category: otc | Type: HUMAN OTC DRUG LABEL
Date: 20231009

ACTIVE INGREDIENTS: ALCOHOL 75 mL/100 mL
INACTIVE INGREDIENTS: GLYCERIN; CARBOMER HOMOPOLYMER, UNSPECIFIED TYPE; WATER; TROLAMINE

55028-015
Wash-free hand sanitizer

Active Ingredient(s)

Ethyl Alcohol 75% v/v

Purpose

Antiseptic

Use

Hand sanitizer to help decrease bacteria on the surface of skin.

Warnings

Flammable, Keep away from source of heat,fire or flame.
For external use only.
Do not apply around the eyes.
Do not use in ears & mouth.

Do not use

Do not apply around the eyes.
Do not use in ears & mouth.

When using this product
Avoid contact with eyes.
If contact occurs, rinse thoroughly with water.

Stop use and ask a doctor if
Irritation or redness develops and lasts.

Keep out of reach of children
Children must be supervised in use of this product.

Directions

Pump enough product into your plams and thoroughly spread on both hands, rub into skin until dry. Children under 6 years should be supervised when using this product.

Other information

Store at temperature below 43°C (110°F)

Inactive ingredients

Water, triethanolamine, glycerin, carbomer